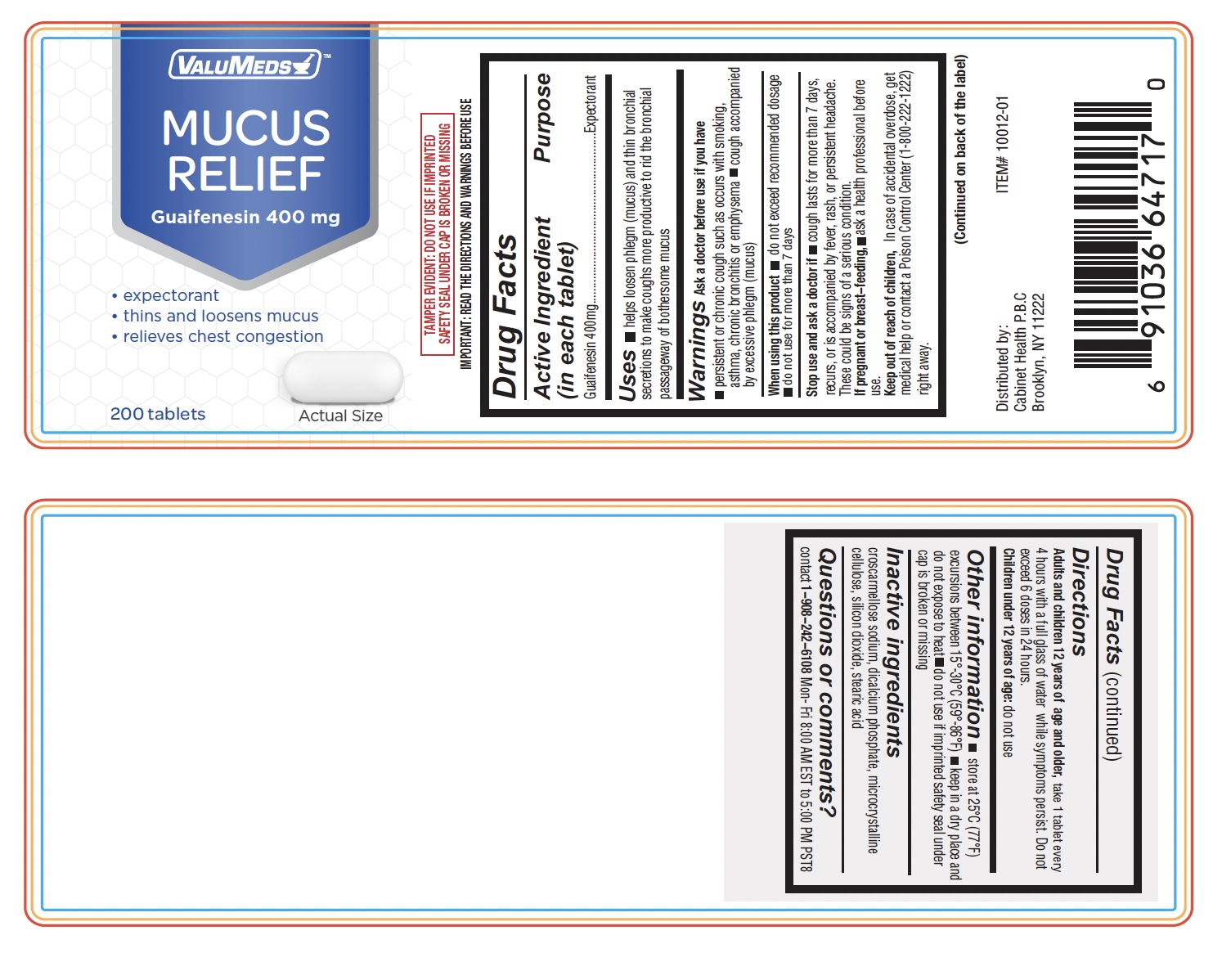 DRUG LABEL: Mucus Relief
NDC: 82725-1012 | Form: TABLET
Manufacturer: Cabinet Health, Inc.
Category: otc | Type: HUMAN OTC DRUG LABEL
Date: 20250707

ACTIVE INGREDIENTS: GUAIFENESIN 400 mg/1 1
INACTIVE INGREDIENTS: SILICON DIOXIDE; MAGNESIUM STEARATE; CELLULOSE, MICROCRYSTALLINE; STEARIC ACID; POVIDONE; MALTODEXTRIN; CROSCARMELLOSE SODIUM

ValuMeds Mucus Relief Caplets Guaifenesin 400mg

Active ingredient (in each tablet)

Guaifenesin 400 mg

Purpose

Expectorant

Uses

- helps loosen phlegm (mucus) and thin bronchial secretions to make coughs more productive to rid the bronchial passageway of bothersome mucus

Warnings

ask a doctor before use if you have

- persistent or chronic cough such as occurs with smoking, asthma, chronic bronchitis or emphysema
- cough accompanied by excessive phlegm (mucus)

When using this product

- do not exceed recommended dosage
- do not use for more than 7 days

Stop use and ask a doctor if

- cough lasts for more than 7 days, recurs, or is accompanied by fever, rash, or persistent headache.

These could be signs of a serious condition.

PREGNANCY OR BREAST FEEDING

If pregnant or breast-feeding,ask a health professional before use.

Keep out of reach of children.

In case of overdose, get medical help or contact a Poison Control Center right away.

Directions:

- adults and children 12 years of age and over:take 1 tablet every 4 hours with a full glass of water while symptoms persist. Do not exceed 6 doses in 24 hours.
- children under 12 years:do not use

Other information

- each tablet contains: sodium 1.24 mg VERY LOW SODIUM
- store at 25°C (77°F) excursions between 15°-30°C (59°-86°F)
- keep in a dry place and do not expose to heat
- read all product information before using
- TAMPER EVIDENT: DO NOT USE IF IMPRINTED SAFETY SEAL UNDER CAP IS BROKEN OR MISSING

Inactive ingredients

colloidal silicon dioxide, magnesium stearate, microcrystalline cellulose, stearic acid, sodium starch glycolate

Questions or Comments

contact 1-908-242-6108 Mon- Fri 8:00 AM EST to 5:00 PM

Principal Display Panel

ValuMeds Mucus Relief Caplets Guaifenesin 400mg (200 Caplets) | Chest Congestion and Decongestant | Thins and Loosens Buildup | Fast Acting

NDC 82725-1012-1